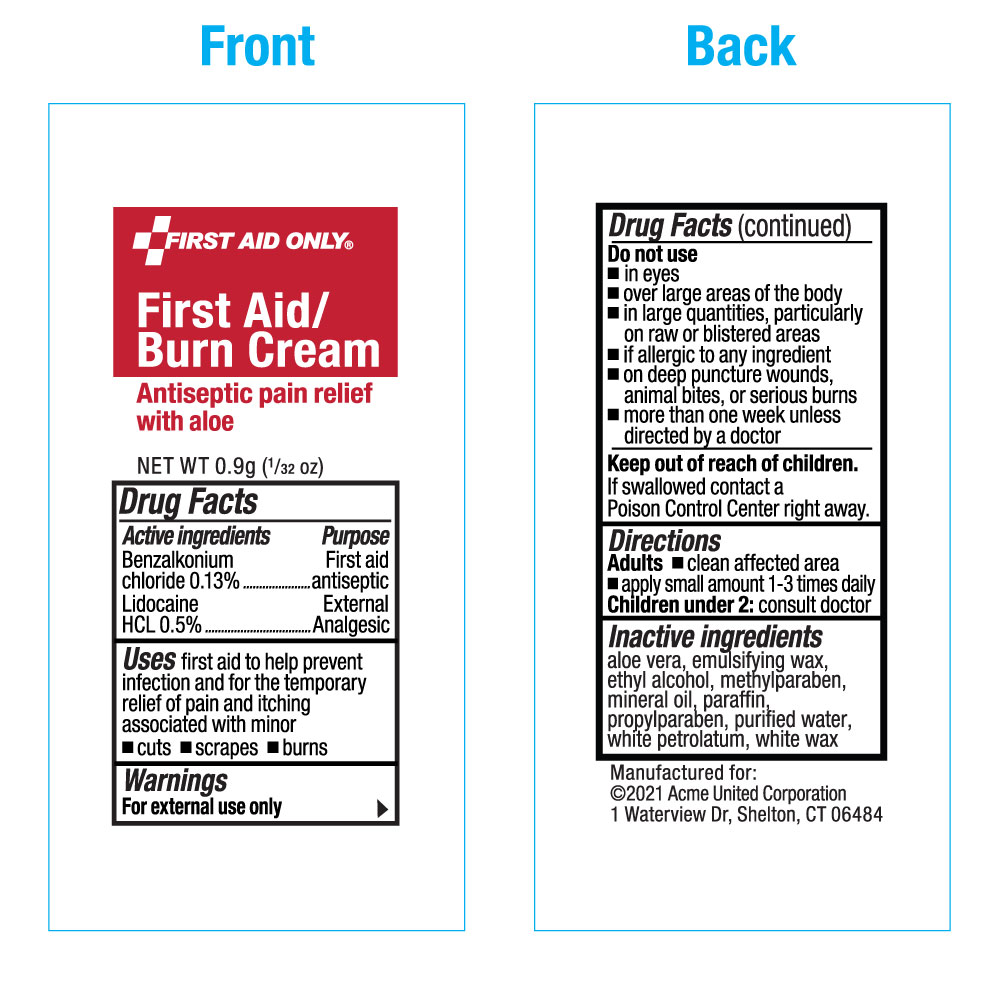 DRUG LABEL: First Aid Only First Aid-Burn
NDC: 0924-5702 | Form: CREAM
Manufacturer: Acme United Corporation
Category: otc | Type: HUMAN OTC DRUG LABEL
Date: 20241218

ACTIVE INGREDIENTS: BENZALKONIUM CHLORIDE 1.3 mg/1 g; LIDOCAINE HYDROCHLORIDE 5 mg/1 g
INACTIVE INGREDIENTS: ALOE VERA LEAF; ALCOHOL; METHYLPARABEN; MINERAL OIL; PARAFFIN; PROPYLPARABEN; WATER; PETROLATUM; WHITE WAX

First Aid Only First Aid-Burn Cream

Drug Facts

Active Ingredients

Benzalkonium Chloride 0.13%

Lidocaine HCl 0.5%

Purpose

First Aid Antiseptic

External Analgesic

Uses

First aid to help prevent infection and for the temporary relief of pain and itching associated with minor

- cuts
- scrapes
- burns.

Warnings

For external use only

Do not use

- in the eyes
- over large areas of the body
- in large quantities, particularly over raw surfaces or blistered areas
- if you are allergic to any of the ingredients
- on deep puncture wounds, animal bites, or serious burns
- more than one week unless directed by a doctor

Keep out of reach of children.

If swallowed contact a Poison Control Center right away.

Directions

- clean affected area
- apply small amount 1-3 times daily
- children under 2: consult doctor

Inactive ingredients

aloe vera, emulsifying wax, ethyl alcohol, methylparaben, mineral oil, paraffin, propylparaben, purified water, white petrolatum, white wax

Packet Label